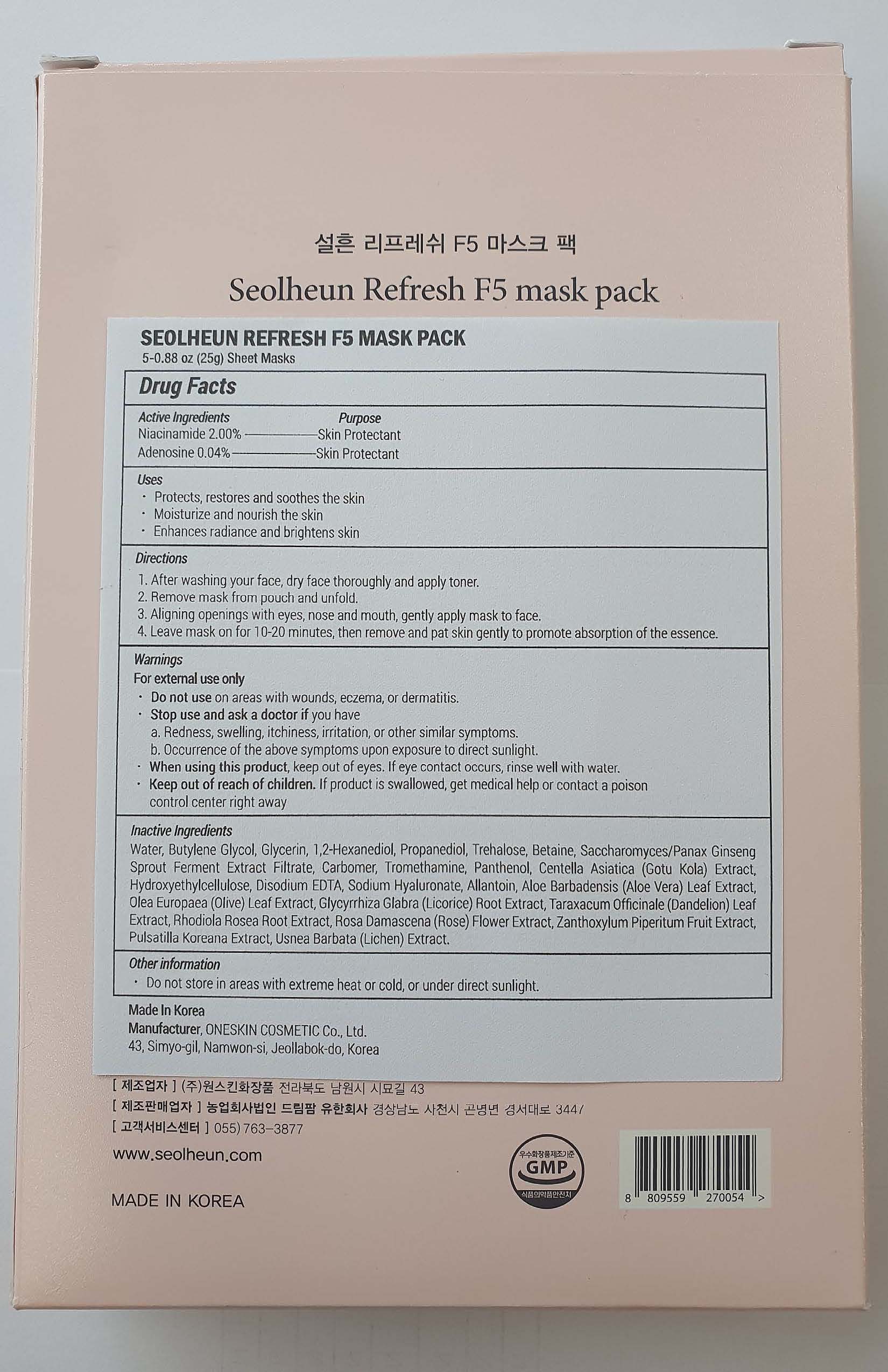 DRUG LABEL: Seolheun Refresh F5 Mask Pack
NDC: 70889-610 | Form: PATCH
Manufacturer: Oneskin Cosmetics Co., Ltd.
Category: otc | Type: HUMAN OTC DRUG LABEL
Date: 20200714

ACTIVE INGREDIENTS: NIACINAMIDE 0.5 g/25 g; ADENOSINE 0.01 g/25 g
INACTIVE INGREDIENTS: GLYCYRRHIZA GLABRA WHOLE; ASIAN GINSENG; BETAINE; WATER; BUTYLENE GLYCOL; HYALURONATE SODIUM; GLYCERIN; ROSA DAMASCENA FLOWERING TOP; OLEA EUROPAEA LEAF

ACTIVE INGREDIENT

Niacinamide 2.00%--------------------Skin Protectant

Adenosine 0.04%----------------------Skin Protectant

PURPOSE

Skin Protectant

INDICATIONS AND USAGE

- Protects, restores and soothes the skin
- Moisturize and nourish the skin
- Enhances radiance and brightens skin

DOSAGE AND ADMINISTRATION

1. After washing your face, dry face thoroughly and apply toner.
2. Remove mask from pouch and unfold.
3. Aligning openings with eyes, nose and mouth, gently apply mask to face.
4. Leave mask on for 10-20 minutes, then remove and pat skin gently to promote absorption

of the essence.

WARNINGS

For external use only

Do not use on areas with wounds, eczema, or dermatitis.

Stop use and ask a doctor if you have

a. Redness, swelling, itchiness, irritation, or other similar symptoms.
b. Occurrence of the above symptoms upon exposure to direct sunlight.

When using this product, keep out of eyes. If eye contact occurs, rinse well with water.
Keep out of reach of children. If product is swallowed, get medical help or contact a poison control center right away

Keep out of reach of children. If product is swallowed, get medical help or contact a poison control center right away

INACTIVE INGREDIENT

Water, Butylene Glycol, Glycerin, 1,2-Hexanediol, Propanediol, Trehalose, Betaine, Saccharomyces/Panax Ginseng Sprout Ferment Extract Filtrate, Carbomer, Tromethamine, Panthenol, Centella Asiatica (Gotu Kola) Extract, Hydroxyethylcellulose, Disodium EDTA, Sodium Hyaluronate, Allantoin, Aloe Barbadensis (Aloe Vera) Leaf Extract, Olea Europaea (Olive) Leaf Extract, Glycyrrhiza Glabra (Licorice) Root Extract, Taraxacum Officinale (Dandelion) Leaf Extract, Rhodiola Rosea Root Extract, Rosa Damascena (Rose) Flower Extract, Zanthoxylum Piperitum Fruit Extract, Pulsatilla Koreana Extract, Usnea Barbata (Lichen) Extract..

OTHER SAFETY INFORMATION

Do not store in areas with extreme heat or cold, or under direct sunlight.